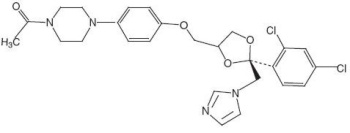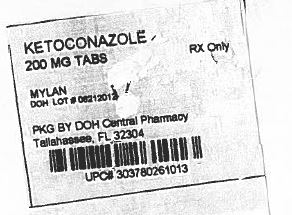 DRUG LABEL: Ketoconazole
NDC: 53808-0842 | Form: TABLET
Manufacturer: State of Florida DOH Central Pharmacy
Category: prescription | Type: HUMAN PRESCRIPTION DRUG LABEL
Date: 20130912

ACTIVE INGREDIENTS: KETOCONAZOLE 200 mg/1 1
INACTIVE INGREDIENTS: SILICON DIOXIDE; LACTOSE MONOHYDRATE; MAGNESIUM STEARATE; CELLULOSE, MICROCRYSTALLINE; POVIDONES; STARCH, CORN

WARNING

When used orally, ketoconazole has been associated with hepatic toxicity, including some fatalities. Patients receiving this drug should be informed by the physician of the risk and should be closely monitored. (See WARNINGS and PRECAUTIONS.)

Coadministration of terfenadine with ketoconazole tablets is contraindicated. Rare cases of serious cardiovascular adverse events, including death, ventricular tachycardia and Torsades de pointes have been observed in patients taking ketoconazole tablets concomitantly with terfenadine, due to increased terfenadine concentrations induced by ketoconazole tablets. (See CONTRAINDICATIONS, WARNINGS, and PRECAUTIONS.)

Pharmacokinetic data indicate that oral ketoconazole inhibits the metabolism of astemizole, resulting in elevated plasma levels of astemizole and its active metabolite desmethylastemizole which may prolong QT intervals. Coadministration of astemizole with ketoconazole tablets is therefore contraindicated. (See CONTRAINDICATIONS, WARNINGS, and PRECAUTIONS.)

Coadministration of cisapride with ketoconazole is contraindicated. Serious cardiovascular adverse events including ventricular tachycardia, ventricular fibrillation and Torsades de pointes have occurred in patients taking ketoconazole concomitantly with cisapride. (See CONTRAINDICATIONS, WARNINGS, and PRECAUTIONS.)

DESCRIPTION

Ketoconazole tablets, USP are a synthetic broad spectrum antifungal agent available in scored white tablets, each containing 200 mg ketoconazole base for oral administration. In addition, each tablet also contains the following inactive ingredients: colloidal silicon dioxide, lactose monohydrate, magnesium stearate, microcrystalline cellulose, povidone and corn starch. Ketoconazole is cis-1-acetyl-4-[4-[[2-(2,4-dichlorophenyl)-2-(1H-imidazol-1-ylmethyl)-1,3-dioxolan-4-yl]methoxyl]phenyl] piperazine.

Ketoconazole, USP is a white to slightly beige, odorless powder, soluble in acids, with a molecular weight of 531.44. Ketoconazole's structural formula and molecular formula are as follows:

C26H28Cl2N4O4

CLINICAL PHARMACOLOGY

Mean peak plasma levels of approximately 3.5 mcg/mL are reached within 1 to 2 hours, following oral administration of a single 200 mg dose taken with a meal. Subsequent plasma elimination is biphasic with a half-life of 2 hours during the first 10 hours and 8 hours thereafter. Following absorption from the gastrointestinal tract, ketoconazole is converted into several inactive metabolites. The major identified metabolic pathways are oxidation and degradation of the imidazole and piperazine rings, oxidative O-dealkylation and aromatic hydroxylation. About 13% of the dose is excreted in the urine, of which 2% to 4% is unchanged drug. The major route of excretion is through the bile into the intestinal tract. In vitro, the plasma protein binding is about 99% mainly to the albumin fraction. Only a negligible proportion of ketoconazole reaches the cerebral-spinal fluid. Ketoconazole is a weak dibasic agent and thus requires acidity for dissolution and absorption.

Ketoconazole tablets are active against clinical infections with Blastomyces dermatitidis, Candida spp., Coccidioides immitis, Histoplasma capsulatum, Paracoccidioides brasiliensis, and Phialophora spp. Ketoconazole tablets are also active against Trichophyton spp., Epidermophyton spp., and Microsporum spp. Ketoconazole is also active in vitro against a variety of fungi and yeast. In animal models, activity has been demonstrated against Candida spp., Blastomyces dermatitidis, Histoplasma capsulatum, Malassezia furfur, Coccidioides immitis, and Cryptococcus neoformans.

Mode of Action

In vitro studies suggest that ketoconazole impairs the synthesis of ergosterol, which is a vital component of fungal cell membranes.

INDICATIONS AND USAGE

Ketoconazole tablets are indicated for the treatment of the following systemic fungal infections: candidiasis, chronic mucocutaneous candidiasis, oral thrush, candiduria, blastomycosis, coccidioidomycosis, histoplasmosis, chromomycosis, and paracoccidioidomycosis. Ketoconazole tablets should not be used for fungal meningitis because it penetrates poorly into the cerebral-spinal fluid.

Ketoconazole tablets are also indicated for the treatment of patients with severe recalcitrant cutaneous dermatophyte infections who have not responded to topical therapy or oral griseofulvin, or who are unable to take griseofulvin.

CONTRAINDICATIONS

Coadministration of terfenadine or astemizole with ketoconazole tablets is contraindicated. (See BOX WARNING, WARNINGS, and PRECAUTIONS.)

Concomitant administration of ketoconazole tablets with cisapride is contraindicated. (See BOX WARNING, WARNINGS and PRECAUTIONS.)

Concomitant administration of ketoconazole tablets with oral triazolam is contraindicated. (See PRECAUTIONS.)

Ketoconazole is contraindicated in patients who have shown hypersensitivity to the drug.

WARNINGS

Hepatotoxicity, primarily of the hepatocellular type, has been associated with the use of ketoconazole tablets, including rare fatalities. The reported incidence of hepatotoxicity has been about 1:10,000 exposed patients, but this probably represents some degree of under-reporting, as is the case for most reported adverse reactions to drugs. The median duration of ketoconazole tablet therapy in patients who developed symptomatic hepatotoxicity was about 28 days, although the range extended to as low as 3 days. The hepatic injury has usually, but not always, been reversible upon discontinuation of ketoconazole tablet treatment. Several cases of hepatitis have been reported in children.

Prompt recognition of liver injury is essential. Liver function tests (such as SGGT, alkaline phosphatase, SGPT, SGOT and bilirubin) should be measured before starting treatment and at frequent intervals during treatment. Patients receiving ketoconazole tablets concurrently with other potentially hepatotoxic drugs should be carefully monitored, particularly those patients requiring prolonged therapy or those who have had a history of liver disease.

Most of the reported cases of hepatic toxicity have to date been in patients treated for onychomycosis. Of 180 patients worldwide developing idiosyncratic liver dysfunction during ketoconazole tablet therapy, 61.3% had onychomycosis and 16.8% had chronic recalcitrant dermatophytoses.

Transient minor elevations in liver enzymes have occurred during treatment with ketoconazole tablets. The drug should be discontinued if these persist, if the abnormalities worsen, or if the abnormalities become accompanied by symptoms of possible liver injury.

In rare cases anaphylaxis has been reported after the first dose. Several cases of hypersensitivity reactions including urticaria have also been reported.

Coadministration of ketoconazole tablets and terfenadine has led to elevated plasma concentrations of terfenadine which may prolong QT intervals, sometimes resulting in life threatening cardiac dysrhythmias. Cases of Torsades de pointes and other serious ventricular dysrhythmias, in rare cases leading to fatality, have been reported among patients taking terfenadine concurrently with ketoconazole tablets. Coadministration of ketoconazole tablets and terfenadine is contraindicated.

Coadministration of astemizole with ketoconazole tablets is contraindicated. (See BOX WARNING, CONTRAINDICATIONS, and PRECAUTIONS.)

Concomitant administration of ketoconazole tablets with cisapride is contraindicated because it has resulted in markedly elevated cisapride plasma concentrations and prolonged QT interval, and has rarely been associated with ventricular arrhythmias and Torsades de pointes. (See BOX WARNING, CONTRAINDICATIONS and PRECAUTIONS.)

In European clinical trials involving 350 patients with metastatic prostatic cancer, 11 deaths were reported within 2 weeks of starting treatment with high doses of ketoconazole tablets (1200 mg/day). It is not possible to ascertain from the information available whether death was related to ketoconazole therapy in these patients with serious underlying disease. However, high doses of ketoconazole tablets are known to suppress adrenal corticosteroid secretion.

In female rats treated 3 to 6 months with ketoconazole at dose levels of 80 mg/kg and higher, increased fragility of long bones, in some cases leading to fracture, was seen. The maximum "no-effect" dose level in these studies was 20 mg/kg (2.5 times the maximum recommended human dose). The mechanism responsible for this phenomenon is obscure. Limited studies in dogs failed to demonstrate such an effect on the metacarpals and ribs.

PRECAUTIONS

General

Ketoconazole tablets have been demonstrated to lower serum testosterone. Once therapy with ketoconazole has been discontinued, serum testosterone levels return to baseline values. Testosterone levels are impaired with doses of 800 mg per day and abolished by 1600 mg per day. Ketoconazole tablets also decrease ACTH induced corticosteroid serum levels at similar high doses. The recommended dose of 200 mg to 400 mg daily should be followed closely.

In four subjects with drug-induced achlorhydria, a marked reduction in ketoconazole absorption was observed. Ketoconazole tablets require acidity for dissolution. If concomitant antacids, anticholinergics, and H2-blockers are needed, they should be given at least 2 hours after administration of ketoconazole tablets. In cases of achlorhydria, the patients should be instructed to dissolve each tablet in 4 mL aqueous solution of 0.2 N HCl. For ingesting the resulting mixture, they should use a drinking straw so as to avoid contact with the teeth. This administration should be followed with a cup of tap water.

Information for Patients

Patients should be instructed to report any signs and symptoms which may suggest liver dysfunction so that appropriate biochemical testing can be done. Such signs and symptoms may include unusual fatigue, anorexia, nausea and/or vomiting, jaundice, dark urine or pale stools. (See WARNINGS.)

Drug Interactions

Ketoconazole is a potent inhibitor of the cytochrome P450 3A4 enzyme system. Coadministration of ketoconazole tablets and drugs primarily metabolized by the cytochrome P450 3A4 enzyme system may result in increased plasma concentrations of the drugs that could increase or prolong both therapeutic and adverse effects. Therefore, unless otherwise specified, appropriate dosage adjustments may be necessary. The following drug interactions have been identified involving ketoconazole tablets and other drugs metabolized by the cytochrome P450 enzyme system.

Ketoconazole tablets inhibit the metabolism of terfenadine, resulting in an increased plasma concentration of terfenadine and a delay in the elimination of its acid metabolite. The increased plasma concentration of terfenadine or its metabolite may result in prolonged QT intervals. (See BOX WARNING, CONTRAINDICATIONS, and WARNINGS.)

Pharmacokinetic data indicate that oral ketoconazole inhibits the metabolism of astemizole, resulting in elevated plasma levels of astemizole and its active metabolite desmethylastemizole which may prolong QT intervals. Coadministration of astemizole with ketoconazole tablets is therefore contraindicated. (See BOX WARNING, CONTRAINDICATIONS, and WARNINGS.)

Human pharmacokinetics data indicate that oral ketoconazole potently inhibits the metabolism of cisapride resulting in a mean 8-fold increase in AUC of cisapride. Data suggest that coadministration of oral ketoconazole and cisapride can result in prolongation of the QT interval on the ECG. Therefore concomitant administration of ketoconazole tablets with cisapride is contraindicated. (See BOX WARNING, CONTRAINDICATIONS, and WARNINGS.)

Ketoconazole tablets may alter the metabolism of cyclosporine, tacrolimus, and methylprednisolone, resulting in elevated plasma concentrations of the latter drugs. Dosage adjustment may be required if cyclosporine, tacrolimus, or methylprednisolone are given concomitantly with ketoconazole tablets.

Coadministration of ketoconazole tablets with midazolam or triazolam has resulted in elevated plasma concentrations of the latter two drugs. This may potentiate and prolong hypnotic and sedative effects, especially with repeated dosing or chronic administration of these agents. These agents should not be used in patients treated with ketoconazole tablets. If midazolam is administered parenterally, special precaution is required since the sedative effect may be prolonged.

Rare cases of elevated plasma concentrations of digoxin have been reported. It is not clear whether this was due to the combination of therapy. It is, therefore, advisable to monitor digoxin concentration in patients receiving ketoconazole.

When taken orally, imidazole compounds like ketoconazole may enhance the anticoagulant effect of coumarin-like drugs. In simultaneous treatment with imidazole drugs and coumarin drugs, the anticoagulant effect should be carefully titrated and monitored.

Because severe hypoglycemia has been reported in patients concomitantly receiving oral miconazole (an imidazole) and oral hypoglycemic agents, such a potential interaction involving the latter agents when used concomitantly with ketoconazole tablets (an imidazole) can not be ruled out.

Concomitant administration of ketoconazole tablets with phenytoin may alter the metabolism of one or both of the drugs. It is suggested to monitor both ketoconazole and phenytoin.

Concomitant administration of rifampin with ketoconazole tablets reduces the blood levels of the latter. INH (Isoniazid) is also reported to affect ketoconazole concentrations adversely. These drugs should not be given concomitantly.

After the coadministration of 200 mg oral ketoconazole twice daily and one 20 mg dose of loratadine to 11 subjects, the AUC and Cmax of loratadine averaged 302% (± 142 S.D.) and 251% (± 68 S.D.), respectively, of those obtained after co-treatment with placebo. The AUC and Cmax of descarboethoxyloratadine, an active metabolite, averaged 155% (± 27 S.D.) and 141% (± 35 S.D.), respectively. However, no related changes were noted in the QTc on ECG taken at 2, 6, and 24 hours after the coadministration. Also, there were no clinically significant differences in adverse events when loratadine was administered with or without ketoconazole.

Rare cases of a disulfiram-like reaction to alcohol have been reported. These experiences have been characterized by flushing, rash, peripheral edema, nausea, and headache. Symptoms resolved within a few hours.

Carcinogenesis, Mutagenesis, Impairment of Fertility

The dominant lethal mutation test in male and female mice revealed that single oral doses of ketoconazole as high as 80 mg/kg produced no mutation in any stage of germ cell development. The Ames Salmonella microsomal activator assay was also negative. A long term feeding study in Swiss Albino mice and in Wistar rats showed no evidence of oncogenic activity.

Teratogenic Effects. Pregnancy Category C

Ketoconazole has been shown to be teratogenic (syndactylia and oligodactylia) in the rat when given in the diet at 80 mg/kg/day (10 times the maximum recommended human dose). However, these effects may be related to maternal toxicity, evidence of which also was seen at this and higher dose levels.

There are no adequate and well controlled studies in pregnant women. Ketoconazole should be used during pregnancy only if the potential benefit justifies the potential risk to the fetus.

Nonteratogenic Effects

Ketoconazole has also been found to be embryotoxic in the rat when given in the diet at doses higher than 80 mg/kg during the first trimester of gestation.

In addition, dystocia (difficult labor) was noted in rats administered oral ketoconazole during the third trimester of gestation. This occurred when ketoconazole was administered at doses higher than 10 mg/kg (higher than 1.25 times the maximum human dose).

It is likely that both the malformations and the embryotoxicity resulting from the administration of oral ketoconazole during gestation are a reflection of the particular sensitivity of the female rat to this drug. For example, the oral LD50 of ketoconazole given by gavage to the female rat is 166 mg/kg whereas in the male rat the oral LD50 is 287 mg/kg.

Nursing Mothers

Since ketoconazole is probably excreted in the milk, mothers who are under treatment should not breast- feed.

Pediatric Use

Ketoconazole tablets have not been systematically studied in children of any age, and essentially no information is available on children under 2 years. Ketoconazole should not be used in pediatric patients unless the potential benefit outweighs the risks.

ADVERSE REACTIONS

In rare cases, anaphylaxis has been reported after the first dose. Several cases of hypersensitivity reactions including urticaria have also been reported. However, the most frequent adverse reactions were nausea and/or vomiting in approximately 3%, abdominal pain in 1.2%, pruritus in 1.5%, and the following in less than 1% of the patients: headache, dizziness, somnolence, fever and chills, photophobia, diarrhea, gynecomastia, impotence, thrombocytopenia, leukopenia, hemolytic anemia, and bulging fontanelles. Oligospermia has been reported in investigational studies with the drug at dosages above those currently approved. Oligospermia has not been reported at dosages up to 400 mg daily, however sperm counts have been obtained infrequently in patients treated with these dosages. Most of these reactions were mild and transient and rarely required discontinuation of ketoconazole tablets. In contrast, the rare occurrences of hepatic dysfunction require special attention (See WARNINGS.)

In worldwide post-marketing experience with ketoconazole tablets there have been rare reports of alopecia, paresthesia, and signs of increased intracranial pressure including bulging fontanelles and papilledema. Hypertriglyceridemia has also been reported but a causal association with ketoconazole is uncertain.

Neuropsychiatric disturbances, including suicidal tendencies and severe depression, have occurred rarely in patients using ketoconazole tablets.

Ventricular dysrhythmias (prolonged QT intervals) have occurred with the concomitant use of terfenadine with ketoconazole tablets. (See BOX WARNING, CONTRAINDICATIONS, and WARNINGS.) Data suggest that coadministration of ketoconazole tablets and cisapride can result in prolongation of the QT interval and has rarely been associated with ventricular arrhythmias. (See CONTRAINDICATIONS, WARNINGS, and PRECAUTIONS.)

OVERDOSAGE

In the event of accidental overdosage, supportive measures, including gastric lavage with sodium bicarbonate, should be employed.

DOSAGE AND ADMINISTRATION

Adults

The recommended starting dose of ketoconazole tablets is a single daily administration of 200 mg (one tablet). In very serious infections or if clinical responsiveness is insufficient within the expected time, the dose of ketoconazole may be increased to 400 mg (two tablets) once daily.

Children

In small numbers of children over 2 years of age, a single daily dose of 3.3 to 6.6 mg/kg has been used. Ketoconazole tablets have not been studied in children under 2 years of age.

There should be laboratory as well as clinical documentation of infection prior to starting ketoconazole tablet therapy. Treatment should be continued until tests indicate that active fungal infection has subsided. Inadequate periods of treatment may yield poor response and lead to early recurrence of clinical symptoms. Minimum treatment for candidiasis is one or two weeks. Patients with chronic mucocutaneous candidiasis usually require maintenance therapy. Minimum treatment for the other indicated systemic mycoses is 6 months.

Minimum treatment for recalcitrant dermatophyte infections is 4 weeks in cases involving glabrous skin. Palmar and plantar infections may respond more slowly. Apparent cures may subsequently recur after discontinuation of therapy in some cases.

HOW SUPPLIED

Ketoconazole Tablets, USP are available containing 200 mg of ketoconazole, USP.

The 200 mg tablet is a white to off-white round tablet debossed with M above the score and 261 below the score on one side of the tablet and blank on the other side.

They are supplied by State of Florida DOH Central Pharmacy as follows:

NDC | Strength | Quantity/Form | Color | Source Prod. Code
53808-0842-1 | 200 mg | 30 Tablets in a Blister Pack | white to off-white | 0378-0261

Store at 20° to 25°C (68° to 77°F). [See USP Controlled Room Temperature.]

Protect from light and moisture.

Mylan Pharmaceuticals Inc.
Morgantown, WV 26505 U.S.A.

www.mylan.com

This Product was Repackaged By:

State of Florida DOH Central Pharmacy
104-2 Hamilton Park Drive
Tallahassee, FL 32304
United States

PACKAGE LABEL

PRINCIPAL DISPLAY PANEL - 200 mg

NDC 53808-0842-1

Ketoconazole
Tablets, USP
200 mg

Rx only 30 TABLETS

Each tablet contains:
Ketoconazole, USP 200 mg

Keep this and all medication
out of the reach of children.

Store at 20° to 25°C (68° to 77°F).
[See USP Controlled Room
Temperature.]

Protect from moisture.

Usual Dosage: See accompanying
prescribing information.